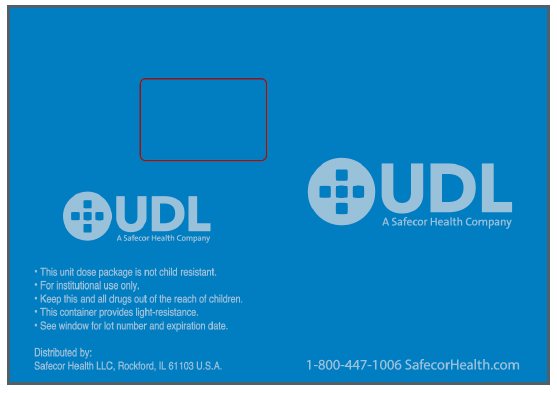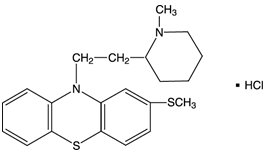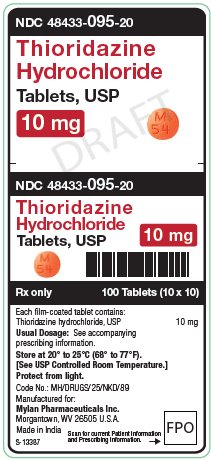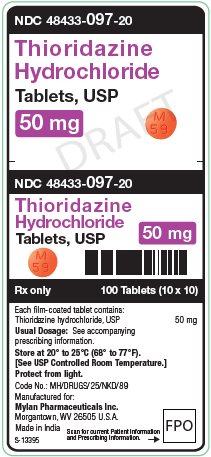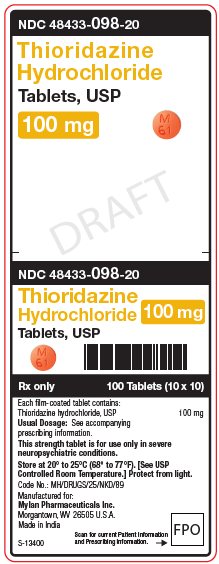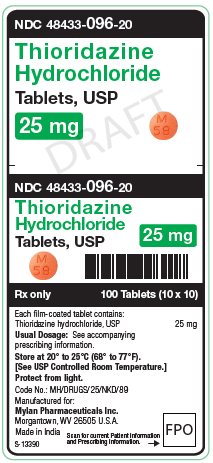 DRUG LABEL: Thioridazine Hydrochloride
NDC: 48433-095 | Form: TABLET, FILM COATED
Manufacturer: Safecor Health LLC
Category: prescription | Type: HUMAN PRESCRIPTION DRUG LABEL
Date: 20260220

ACTIVE INGREDIENTS: THIORIDAZINE HYDROCHLORIDE 10 mg/1 1
INACTIVE INGREDIENTS: SILICON DIOXIDE; CROSCARMELLOSE SODIUM; FD&C YELLOW NO. 6; HYDROXYPROPYL CELLULOSE, UNSPECIFIED; HYPROMELLOSE, UNSPECIFIED; MAGNESIUM STEARATE; MICROCRYSTALLINE CELLULOSE; POLYETHYLENE GLYCOL, UNSPECIFIED; SODIUM LAURYL SULFATE; TITANIUM DIOXIDE

WARNING

Thioridazine has been shown to prolong the QTc interval in a dose related manner, and drugs with this potential, including thioridazine, have been associated with Torsades de pointes type arrhythmias and sudden death. Due to its potential for significant, possibly life threatening, proarrhythmic effects, thioridazine should be reserved for use in the treatment of schizophrenic patients who fail to show an acceptable response to adequate courses of treatment with other antipsychotic drugs, either because of insufficient effectiveness or the inability to achieve an effective dose due to intolerable adverse effects from those drugs (see WARNINGS, CONTRAINDICATIONS, and INDICATIONS).

Increased Mortality in Elderly Patients with Dementia-Related Psychosis

Elderly patients with dementia-related psychosis treated with antipsychotic drugs are at an increased risk of death. Analyses of seventeen placebo-controlled trials (modal duration of 10 weeks), largely in patients taking atypical antipsychotic drugs, revealed a risk of death in drug-treated patients of between 1.6 to 1.7 times the risk of death in placebo-treated patients. Over the course of a typical 10-week controlled trial, the rate of death in drug-treated patients was about 4.5%, compared to a rate of about 2.6% in the placebo group. Although the causes of death were varied, most of the deaths appeared to be either cardiovascular (e.g., heart failure, sudden death) or infectious (e.g., pneumonia) in nature. Observational studies suggest that, similar to atypical antipsychotic drugs, treatment with conventional antipsychotic drugs may increase mortality. The extent to which the findings of increased mortality in observational studies may be attributed to the antipsychotic drug as opposed to some characteristic(s) of the patients is not clear. Thioridazine hydrochloride is not approved for the treatment of patients with dementia-related psychosis (see WARNINGS).

DESCRIPTION

Thioridazine hydrochloride is 2-methylmercapto-10-[2-(N-methyl-2-piperidyl) ethyl] phenothiazine. Its structural formula, molecular weight and molecular formula are:

Thioridazine hydrochloride, USP is available as tablets for oral administration containing 10 mg, 25 mg, 50 mg or 100 mg.

Each tablet for oral administration contains the following inactive ingredients: colloidal silicon dioxide, croscarmellose sodium, FD&C Yellow No. 6 Aluminum Lake, hydroxypropyl cellulose, hypromellose, magnesium stearate, microcrystalline cellulose, polyethylene glycol, sodium lauryl sulfate and titanium dioxide.

CLINICAL PHARMACOLOGY

The basic pharmacological activity of thioridazine is similar to that of other phenothiazines, but is associated with minimal extrapyramidal stimulation.

However, thioridazine has been shown to prolong the QTc interval in a dose dependent fashion. This effect may increase the risk of serious, potentially fatal, ventricular arrhythmias, such as Torsades de pointes type arrhythmias. Due to this risk, thioridazine is indicated only for schizophrenic patients who have not been responsive to or cannot tolerate other antipsychotic agents (see WARNINGSand CONTRAINDICATIONS). However, the prescriber should be aware that thioridazine has not been systematically evaluated in controlled trials in treatment refractory schizophrenic patients and its efficacy in such patients is unknown.

INDICATIONS AND USAGE

Thioridazine hydrochloride tablets are indicated for the management of schizophrenic patients who fail to respond adequately to treatment with other antipsychotic drugs. Due to the risk of significant, potentially life threatening, proarrhythmic effects with thioridazine treatment, thioridazine hydrochloride tablets should be used only in patients who have failed to respond adequately to treatment with appropriate courses of other antipsychotic drugs, either because of insufficient effectiveness or the inability to achieve an effective dose due to intolerable adverse effects from those drugs. Consequently, before initiating treatment with thioridazine hydrochloride tablets, it is strongly recommended that a patient be given at least two trials, each with a different antipsychotic drug product, at an adequate dose, and for an adequate duration (see WARNINGSand CONTRAINDICATIONS).

However, the prescriber should be aware that thioridazine hydrochloride tablets have not been systematically evaluated in controlled trials in treatment refractory schizophrenic patients and its efficacy in such patients is unknown.

CONTRAINDICATIONS

Thioridazine hydrochloride tablet use should be avoided in combination with other drugs that are known to prolong the QTc interval and in patients with congenital long QT syndrome or a history of cardiac arrhythmias.

Reduced cytochrome P450 2D6 isozyme activity drugs that inhibit this isozyme (e.g., fluoxetine and paroxetine) and certain other drugs (e.g., fluvoxamine, propranolol, and pindolol) appear to appreciably inhibit the metabolism of thioridazine. The resulting elevated levels of thioridazine would be expected to augment the prolongation of the QTc interval associated with thioridazine and may increase the risk of serious, potentially fatal, cardiac arrhythmias, such as Torsades de pointes type arrhythmias. Such an increased risk may result also from the additive effect of coadministering thioridazine with other agents that prolong the QTc interval. Therefore, thioridazine is contraindicated with these drugs as well as in patients, comprising about 7% of the normal population, who are known to have a genetic defect leading to reduced levels of activity of P450 2D6 (see WARNINGSand PRECAUTIONS).

In common with other phenothiazines, thioridazine is contraindicated in severe central nervous system depression or comatose states from any cause including drug induced central nervous system depression (see WARNINGS). It should also be noted that hypertensive or hypotensive heart disease of extreme degree is a contraindication of phenothiazine administration.

WARNINGS

Increased Mortality in Elderly Patients with Dementia-Related Psychosis

Elderly patients with dementia-related psychosis treated with antipsychotic drugs are at an increased risk of death. Thioridazine hydrochloride is not approved for the treatment of patients with dementia-related psychosis (see BOXED WARNING).

Potential for Proarrhythmic Effects

DUE TO THE POTENTIAL FOR SIGNIFICANT, POSSIBLY LIFE THREATENING, PROARRHYTHMIC EFFECTS WITH THIORIDAZINE TREATMENT, THIORIDAZINE SHOULD BE RESERVED FOR USE IN THE TREATMENT OF SCHIZOPHRENIC PATIENTS WHO FAIL TO SHOW AN ACCEPTABLE RESPONSE TO ADEQUATE COURSES OF TREATMENT WITH OTHER ANTIPSYCHOTIC DRUGS, EITHER BECAUSE OF INSUFFICIENT EFFECTIVENESS OR THE INABILITY TO ACHIEVE AN EFFECTIVE DOSE DUE TO INTOLERABLE ADVERSE EFFECTS FROM THOSE DRUGS. CONSEQUENTLY, BEFORE INITIATING TREATMENT WITH THIORIDAZINE, IT IS STRONGLY RECOMMENDED THAT A PATIENT BE GIVEN AT LEAST TWO TRIALS, EACH WITH A DIFFERENT ANTIPSYCHOTIC DRUG PRODUCT, AT AN ADEQUATE DOSE, AND FOR AN ADEQUATE DURATION. THIORIDAZINE HAS NOT BEEN SYSTEMATICALLY EVALUATED IN CONTROLLED TRIALS IN THE TREATMENT OF REFRACTORY SCHIZOPHRENIC PATIENTS AND ITS EFFICACY IN SUCH PATIENTS IS UNKNOWN.

A crossover study in nine healthy males comparing single doses of thioridazine 10 mg and 50 mg with placebo demonstrated a dose related prolongation of the QTc interval. The mean maximum increase in QTc interval following the 50 mg dose was about 23 msec; greater prolongation may be observed in the clinical treatment of unscreened patients.

Prolongation of the QTc interval has been associated with the ability to cause Torsades de pointes type arrhythmias, a potentially fatal polymorphic ventricular tachycardia, and sudden death. There are several published case reports of Torsades de pointes and sudden death associated with thioridazine treatment. A causal relationship between these events and thioridazine therapy has not been established but, given the ability of thioridazine to prolong the QTc interval, such a relationship is possible.

Certain circumstances may increase the risk of Torsades de pointes and/or sudden death in association with the use of drugs that prolong the QTc interval, including 1) bradycardia, 2) hypokalemia, 3) concomitant use of other drugs that prolong the QTc interval, 4) presence of congenital prolongation of the QT interval, and 5) for thioridazine in particular, its use in patients with reduced activity of P450 2D6 or its coadministration with drugs that may inhibit P450 2D6 or by some other mechanism interfere with the clearance of thioridazine (see CONTRAINDICATIONSand PRECAUTIONS).

It is recommended that patients being considered for thioridazine treatment have a baseline ECG performed and serum potassium levels measured. Serum potassium should be normalized before initiating treatment and patients with a QTc interval greater than 450 msec should not receive thioridazine treatment. It may also be useful to periodically monitor ECG’s and serum potassium during thioridazine treatment, especially during a period of dose adjustment. Thioridazine should be discontinued in patients who are found to have a QTc interval over 500 msec.

Patients taking thioridazine who experience symptoms that may be associated with the occurrence of Torsades de pointes (e.g., dizziness, palpitations, or syncope) may warrant further cardiac evaluation; in particular, Holter monitoring should be considered.

Tardive Dyskinesia

Tardive dyskinesia, a syndrome consisting of potentially irreversible, involuntary, dyskinetic movements may develop in patients treated with antipsychotic drugs. Although the prevalence of the syndrome appears to be highest among the elderly, especially elderly women, it is impossible to rely upon prevalence estimates to predict, at the inception of antipsychotic treatment, which patients are likely to develop the syndrome. Whether antipsychotic drug products differ in their potential to cause tardive dyskinesia is unknown.

Both the risk of developing the syndrome and the likelihood that it will become irreversible are believed to increase as the duration of treatment and the total cumulative dose of antipsychotic drugs administered to the patient increase. However, the syndrome can develop, although much less commonly, after relatively brief treatment periods at low doses.

There is no known treatment for established cases of tardive dyskinesia, although the syndrome may remit, partially or completely, if antipsychotic treatment is withdrawn. Antipsychotic treatment itself, however, may suppress (or partially suppress) the signs and symptoms of the syndrome and thereby may possibly mask the underlying disease process. The effect that symptomatic suppression has upon the long-term course of the syndrome is unknown.

Given these considerations, antipsychotics should be prescribed in a manner that is most likely to minimize the occurrence of tardive dyskinesia. Chronic antipsychotic treatment should generally be reserved for patients who suffer from a chronic illness that, 1) is known to respond to antipsychotic drugs, and, 2) for whom alternative, equally effective, but potentially less harmful treatments are notavailable or appropriate. In patients who do require chronic treatment, the smallest dose and the shortest duration of treatment producing a satisfactory clinical response should be sought. The need for continued treatment should be reassessed periodically.

If signs and symptoms of tardive dyskinesia appear in a patient on antipsychotics, drug discontinuation should be considered. However, some patients may require treatment despite the presence of the syndrome.

(For further information about the description of tardive dyskinesia and its clinical detection, please refer to the sections on Information for Patientsand ADVERSE REACTIONS.)

It has been suggested in regard to phenothiazines in general, that people who have demonstrated a hypersensitivity reaction (e.g., blood dyscrasias, jaundice) to one may be more prone to demonstrate a reaction to others. Attention should be paid to the fact that phenothiazines are capable of potentiating central nervous system depressants (e.g., anesthetics, opiates, alcohol, etc.) as well as atropine and phosphorus insecticides. Physicians should carefully consider benefit versus risk when treating less severe disorders.

Reproductive studies in animals and clinical experience to date have failed to show a teratogenic effect with thioridazine. However, in view of the desirability of keeping the administration of all drugs to a minimum during pregnancy, thioridazine should be given only when the benefits derived from treatment exceed the possible risks to mother and fetus.

Pregnancy

Nonteratogenic Effects

Neonates exposed to antipsychotic drugs, during the third trimester of pregnancy are at risk for extrapyramidal and/or withdrawal symptoms following delivery. There have been reports of agitation, hypertonia, hypotonia, tremor, somnolence, respiratory distress and feeding disorder in these neonates. These complications have varied in severity; while in some cases symptoms have been self-limited, in other cases neonates have required intensive care unit support and prolonged hospitalization.

Thioridazine hydrochloride should be used during pregnancy only if the potential benefit justifies the potential risk to the fetus.

Neuroleptic Malignant Syndrome (NMS)

A potentially fatal symptom complex sometimes referred to as Neuroleptic Malignant Syndrome (NMS) has been reported in association with antipsychotic drugs. Clinical manifestations of NMS are hyperpyrexia, muscle rigidity, altered mental status, and evidence of autonomic instability (irregular pulse or blood pressure, tachycardia, diaphoresis, and cardiac dysrhythmias).

The diagnostic evaluation of patients with this syndrome is complicated. In arriving at a diagnosis, it is important to identify cases where the clinical presentation includes both serious medical illness (e.g., pneumonia, systemic infection, etc.) and untreated or inadequately treated extrapyramidal signs and symptoms (EPS). Other important considerations in the differential diagnosis include central anticholinergic toxicity, heat stroke, drug fever, and primary central nervous system (CNS) pathology.

The management of NMS should include, 1) immediate discontinuation of antipsychotic drugs and other drugs not essential to concurrent therapy, 2) intensive symptomatic treatment and medical monitoring, and 3) treatment of any concomitant serious medical problems for which specific treatments are available. There is no general agreement about specific pharmacological treatment regimens for uncomplicated NMS.

If a patient requires antipsychotic drug treatment after recovery from NMS, the potential reintroduction of drug therapy should be carefully considered. The patient should be carefully monitored, since recurrences of NMS have been reported.

Falls

Thioridazine hydrochloride tablets may cause somnolence, postural hypotension, motor and sensory instability, which may lead to falls and, consequently, fractures or other injuries. For patients with diseases, conditions, or medications that could exacerbate these effects, complete fall risk assessments when initiating antipsychotic treatment and recurrently for patients on long-term antipsychotic therapy.

Central Nervous System Depressants

As in the case of other phenothiazines, thioridazine is capable of potentiating central nervous system depressants (e.g., alcohol, anesthetics, barbiturates, narcotics, opiates, other psychoactive drugs, etc.) as well as atropine and phosphorus insecticides. Severe respiratory depression and respiratory arrest have been reported when a patient was given a phenothiazine and a concomitant high dose of a barbiturate.

PRECAUTIONS

Leukopenia and/or agranulocytosis and convulsive seizures have been reported but are infrequent. In schizophrenic patients with epilepsy, anticonvulsant medication should be maintained during treatment with thioridazine. Pigmentary retinopathy, which has been observed primarily in patients taking larger than recommended doses, is characterized by diminution of visual acuity, brownish coloring of vision, and impairment of night vision; examination of the fundus discloses deposits of pigment. The possibility of this complication may be reduced by remaining within the recommended limits of dosage.

Where patients are participating in activities requiring complete mental alertness (e.g., driving) it is advisable to administer the phenothiazines cautiously and to increase the dosage gradually. Female patients appear to have a greater tendency to orthostatic hypotension than male patients. The administration of epinephrine should be avoided in the treatment of drug-induced hypotension in view of the fact that phenothiazines may induce a reversed epinephrine effect on occasion. Should a vasoconstrictor be required, the most suitable are levarterenol and phenylephrine.

Antipsychotic drugs elevate prolactin levels; the elevation persists during chronic administration. Tissue culture experiments indicate that approximately one-third of human breast cancers are prolactin dependent in vitro, a factor of potential importance if the prescription of these drugs is contemplated in a patient with a previously detected breast cancer. Although disturbances such as galactorrhea, amenorrhea, gynecomastia, and impotence have been reported, the clinical significance of elevated serum prolactin levels is unknown for most patients. An increase in mammary neoplasms has been found in rodents after chronic administration of neuroleptic drugs. Published epidemiologic studies have shown inconsistent results when exploring the association between hyperprolactinemia and breast cancer.

Drug Interactions

Reduced cytochrome P450 2D6 isozyme activity, drugs which inhibit this isozyme (e.g., fluoxetine and paroxetine), and certain other drugs (e.g., fluvoxamine, propranolol, and pindolol) appear to appreciably inhibit the metabolism of thioridazine. The resulting elevated levels of thioridazine would be expected to augment the prolongation of the QTc interval associated with thioridazine and may increase the risk of serious, potentially fatal, cardiac arrhythmias, such as Torsades de pointes type arrhythmias. Such an increased risk may result also from the additive effect of coadministering thioridazine with other agents that prolong the QTc interval. Therefore, thioridazine is contraindicated with these drugs as well as in patients, comprising about 7% of the normal population, who are known to have a genetic defect leading to reduced levels of activity of P450 2D6 (see WARNINGSand CONTRAINDICATIONS).

Drugs That Inhibit Cytochrome P450 2D6

In a study of 19 healthy male subjects, which included 6 slow and 13 rapid hydroxylators of debrisoquin, a single 25 mg oral dose of thioridazine produced a 2.4-fold higher Cmaxand a 4.5-fold higher AUC for thioridazine in the slow hydroxylators compared to rapid hydroxylators. The rate of debrisoquin hydroxylation is felt to depend on the level of cytochrome P450 2D6 isozyme activity. Thus, this study suggests that drugs that inhibit P450 2D6 or the presence of reduced activity levels of this isozyme will produce elevated plasma levels of thioridazine. Therefore, the coadministration of drugs that inhibit P450 2D6 with thioridazine and the use of thioridazine in patients known to have reduced activity of P450 2D6 are contraindicated.

Drugs That Reduce the Clearance of Thioridazine Through Other Mechanisms

Fluvoxamine

The effect of fluvoxamine (25 mg b.i.d. for one week) on thioridazine steady-state concentration was evaluated in ten male inpatients with schizophrenia. Concentrations of thioridazine and its two active metabolites, mesoridazine and sulforidazine, increased 3-fold following coadministration of fluvoxamine. Fluvoxamine and thioridazine should not be coadministered.

Propranolol

Concurrent administration of propranolol (100 mg to 800 mg daily) has been reported to produce increases in plasma levels of thioridazine (approximately 50% to 400%) and its metabolites (approximately 80% to 300%). Propranolol and thioridazine should not be coadministered.

Pindolol

Concurrent administration of pindolol and thioridazine have resulted in moderate, dose related increases in the serum levels of thioridazine and two of its metabolites, as well as higher than expected serum pindolol levels. Pindolol and thioridazine should not be coadministered.

Drugs That Prolong the QTc Interval

There are no studies of the coadministration of thioridazine and other drugs that prolong the QTc interval. However, it is expected that such coadministration would produce additive prolongation of the QTc interval and, thus, such use is contraindicated.

Information for Patients

Patients should be informed that thioridazine has been associated with potentially fatal heart rhythm disturbances. The risk of such events may be increased when certain drugs are given together with thioridazine. Therefore, patients should inform the prescriber that they are receiving thioridazine treatment before taking any new medication.

Given the likelihood that some patients exposed chronically to antipsychotics will develop tardive dyskinesia, it is advised that all patients in whom chronic use is contemplated be given, if possible, full information about this risk. The decision to inform patients and/or their guardians must obviously take into account the clinical circumstances and the competency of the patient to understand the information provided.

Pediatric Use

See DOSAGE AND ADMINISTRATION: Pediatric Patients.

Leukopenia, Neutropenia and Agranulocytosis

In clinical trial and post-marketing experience, events of leukopenia/neutropenia and agranulocytosis have been reported temporally related to antipsychotic agents.

Possible risk factors for leukopenia/neutropenia include preexisting low white blood cell count (WBC) and history of drug induced leukopenia/neutropenia. Patients with a preexisting low WBC or a history of drug induced leukopenia/neutropenia should have their complete blood count (CBC) monitored frequently during the first few months of therapy and should discontinue Thioridazine Hydrochloride Tablets at the first sign of a decline in WBC in the absence of other causative factors.

Patients with neutropenia should be carefully monitored for fever or other symptoms or signs of infection and treated promptly if such symptoms occur. Patients with severe neutropenia (absolute neutrophil count < 1000/mm^3) should discontinue Thioridazine Hydrochloride Tablets and have their WBC followed until recovery.

ADVERSE REACTIONS

In the recommended dosage ranges with thioridazine hydrochloride most side effects are mild and transient.

Central Nervous System

Drowsiness may be encountered on occasion, especially where large doses are given early in treatment. Generally, this effect tends to subside with continued therapy or a reduction in dosage. Pseudoparkinsonism and other extrapyramidal symptoms may occur but are infrequent. Nocturnal confusion, hyperactivity, lethargy, psychotic reactions, restlessness, and headache have been reported but are extremely rare.

Autonomic Nervous System

Dryness of mouth, blurred vision, constipation, nausea, vomiting, diarrhea, nasal stuffiness, and pallor have been seen.

Endocrine System

Galactorrhea, breast engorgement, amenorrhea, inhibition of ejaculation, and peripheral edema have been described.

Skin

Dermatitis and skin eruptions of the urticarial type have been observed infrequently. Photosensitivity is extremely rare.

Cardiovascular System

Thioridazine produces a dose related prolongation of the QTc interval, which is associated with the ability to cause Torsades de pointes type arrhythmias, a potentially fatal polymorphic ventricular tachycardia, and sudden death (see WARNINGS). Both Torsades de pointes type arrhythmias and sudden death have been reported in association with thioridazine. A causal relationship between these events and thioridazine therapy has not been established but, given the ability of thioridazine to prolong the QTc interval, such a relationship is possible. Other ECG changes have been reported (see Phenothiazine Derivatives: Cardiovascular Effects).

Other

Rare cases described as parotid swelling have been reported following administration of thioridazine.

Post Introduction Reports

These are voluntary reports of adverse events temporally associated with thioridazine that were received since marketing, and there may be no causal relationship between thioridazine use and these events: priapism.

Phenothiazine Derivatives

It should be noted that efficacy, indications, and untoward effects have varied with the different phenothiazines. It has been reported that old age lowers the tolerance for phenothiazines. The most common neurological side effects in these patients are parkinsonism and akathisia. There appears to be an increased risk of agranulocytosis and leukopenia in the geriatric population. The physician should be aware that the following have occurred with one or more phenothiazines and should be considered whenever one of these drugs is used:

Autonomic Reactions: Miosis, obstipation, anorexia, paralytic ileus.

Cutaneous Reactions: Erythema, exfoliative dermatitis, contact dermatitis.

Blood Dyscrasias: Agranulocytosis, leukopenia, eosinophilia, thrombocytopenia, anemia, aplastic anemia, pancytopenia.

Allergic Reactions: Fever, laryngeal edema, angioneurotic edema, asthma.

Hepatotoxicity:Jaundice, biliary stasis.

Cardiovascular Effects: Changes in the terminal portion of the electrocardiogram to include prolongation of the QT interval, depression and inversion of the T wave, and the appearance of a wave tentatively identified as a bifid T wave or a U wave have been observed in patients receiving phenothiazines, including thioridazine. To date, these appear to be due to altered repolarization, not related to myocardial damage, and reversible. Nonetheless, significant prolongation of the QT interval has been associated with serious ventricular arrhythmias and sudden death (see WARNINGS). Hypotension, rarely resulting in cardiac arrest, has been reported.

Extrapyramidal Symptoms: Akathisia, agitation, motor restlessness, dystonic reactions, trismus, torticollis, opisthotonus, oculogyric crises, tremor, muscular rigidity, akinesia.

Tardive Dyskinesia: Chronic use of antipsychotics may be associated with the development of tardive dyskinesia. The salient features of this syndrome are described in the WARNINGSsection and subsequently.

The syndrome is characterized by involuntary choreoathetoid movements which variously involve the tongue, face, mouth, lips, or jaw (e.g., protrusion of the tongue, puffing of cheeks, puckering of the mouth, chewing movements), trunk, and extremities. The severity of the syndrome and the degree of impairment produced vary widely.

The syndrome may become clinically recognizable either during treatment, upon dosage reduction, or upon withdrawal of treatment. Movements may decrease in intensity and may disappear altogether if further treatment with antipsychotics is withheld. It is generally believed that reversibility is more likely after short rather than long-term antipsychotic exposure. Consequently, early detection of tardive dyskinesia is important. To increase the likelihood of detecting the syndrome at the earliest possible time, the dosage of antipsychotic drug should be reduced periodically (if clinically possible) and the patient observed for signs of the disorder. This maneuver is critical, for antipsychotic drugs may mask the signs of the syndrome.

Neuroleptic Malignant Syndrome (NMS): Chronic use of antipsychotics may be associated with the development of Neuroleptic Malignant Syndrome. The salient features of this syndrome are described in the WARNINGSsection and subsequently. Clinical manifestations of NMS are hyperpyrexia, muscle rigidity, altered mental status, and evidence of autonomic instability (irregular pulse or blood pressure, tachycardia, diaphoresis, and cardiac dysrhythmias).

Endocrine Disturbances: Menstrual irregularities, altered libido, gynecomastia, lactation, weight gain, edema. False positive pregnancy tests have been reported.

Urinary Disturbances: Retention, incontinence.

Others: Hyperpyrexia. Behavioral effects suggestive of a paradoxical reaction have been reported. These include excitement, bizarre dreams, aggravation of psychoses, and toxic confusional states. More recently, a peculiar skin-eye syndrome has been recognized as a side effect following long-term treatment with phenothiazines. This reaction is marked by progressive pigmentation of areas of the skin or conjunctiva and/or accompanied by discoloration of the exposed sclera and cornea. Opacities of the anterior lens and cornea described as irregular or stellate in shape have also been reported. Systemic lupus erythematosus-like syndrome.

OVERDOSAGE

Many of the symptoms observed are extensions of the side effects described under ADVERSE REACTIONS. Thioridazine can be toxic in overdose, with cardiac toxicity being of particular concern. Frequent ECG and vital sign monitoring of overdosed patients is recommended. Observation for several days may be required because of the risk of delayed effects.

Signs and Symptoms

Effects and clinical complications of acute overdose involving phenothiazines may include:

Cardiovascular: Cardiac arrhythmias, hypotension, shock, ECG changes, increased QT and PR intervals, non-specific ST and T wave changes, bradycardia, sinus tachycardia, atrioventricular block, ventricular tachycardia, ventricular fibrillation, Torsades de pointes, myocardial depression.

Central Nervous System: Sedation, extrapyramidal effects, confusion, agitation, hypothermia, hyperthermia, restlessness, seizures, areflexia, coma.

Autonomic Nervous System: Mydriasis, miosis, dry skin, dry mouth, nasal congestion, urinary retention, blurred vision.

Respiratory: Respiratory depression, apnea, pulmonary edema.

Gastrointestinal: Hypomotility, constipation, ileus.

Renal: Oliguria, uremia.

Toxic dose and blood concentration ranges for the phenothiazines have not been firmly established. It has been suggested that the toxic blood concentration range for thioridazine begins at 1 mg/dL, and 2 to 8 mg/dL is the lethal concentration range.

Treatment

An airway must be established and maintained. Adequate oxygenation and ventilation must be ensured.

Cardiovascular monitoring should commence immediately and should include continuous electrocardiographic monitoring to detect possible arrhythmias. Treatment may include one or more of the following therapeutic interventions: correction of electrolyte abnormalities and acid-base balance, lidocaine, phenytoin, isoproterenol, ventricular pacing, and defibrillation. Disopyramide, procainamide, and quinidine may produce additive QT-prolonging effects when administered to patients with acute overdosage of thioridazine and should be avoided (see WARNINGSand CONTRAINDICATIONS). Caution must be exercised when administering lidocaine, as it may increase the risk of developing seizures.

Treatment of hypotension may require intravenous fluids and vasopressors. Phenylephrine, levarterenol, or metaraminol are the appropriate pressor agents for use in the management of refractory hypotension. The potent α adrenergic blocking properties of the phenothiazines makes the use of vasopressors with mixed α and ß adrenergic agonist properties inappropriate, including epinephrine and dopamine. Paradoxical vasodilation may result. In addition, it is reasonable to expect that the α adrenergic-blocking properties of bretylium might be additive to those of thioridazine, resulting in problematic hypotension.

In managing overdosage, the physician should always consider the possibility of multiple drug involvement. Gastric lavage and repeated doses of activated charcoal should be considered. Induction of emesis is less preferable to gastric lavage because of the risk of dystonia and the potential for aspiration of vomitus. Emesis should not be induced in patients expected to deteriorate rapidly, or those with impaired consciousness.

Acute extrapyramidal symptoms may be treated with diphenhydramine hydrochloride or benztropine mesylate.

Avoid the use of barbiturates when treating seizures, as they may potentiate phenothiazine-induced respiratory depression.

Forced diuresis, hemoperfusion, hemodialysis and manipulation of urine pH are of unlikely benefit in the treatment of phenothiazine overdose due to their large volume of distribution and extensive plasma protein binding.

Up-to-date information about the treatment of overdose can often be obtained from a certified Regional Poison Control Center. Telephone numbers of certified Regional Poison Control Centers are listed in the Physicians’ Desk Reference®**.

DOSAGE AND ADMINISTRATION

Since thioridazine hydrochloride tablets are associated with a dose related prolongation of the QTc interval, which is a potentially life threatening event, its use should be reserved for schizophrenic patients who fail to respond adequately to treatment with other antipsychotic drugs. Dosage must be individualized and the smallest effective dosage should be determined for each patient (see INDICATIONSand WARNINGS).

Adults

The usual starting dose for adult schizophrenic patients is 50 mg to 100 mg three times a day, with a gradual increment to a maximum of 800 mg daily if necessary. Once effective control of symptoms has been achieved, the dosage may be reduced gradually to determine the minimum maintenance dose. The total daily dosage ranges from 200 mg to 800 mg, divided into two to four doses.

Pediatric Patients

For pediatric patients with schizophrenia who are unresponsive to other agents, the recommended initial dose is 0.5 mg/kg/day given in divided doses. Dosage may be increased gradually until optimum therapeutic effect is obtained or the maximum dose of 3 mg/kg/day has been reached.

HOW SUPPLIED

Thioridazine Hydrochloride Tablets, USP are available containing 10 mg, 25 mg, 50 mg or 100 mg of thioridazine hydrochloride, USP.

The 10 mg tablets are orange film-coated, round, unscored tablets debossed with Mover 54on one side and 10on the other side. They are available as follows:

NDC 48433-095-20 – Unit dose blister packages of 100 (10 cards of 10 tablets each).

The 25 mg tablets are orange film-coated, round, unscored tablets debossed with Mover 58on one side and 25on the other side. They are available as follows:

NDC 48433-096-20 – Unit dose blister packages of 100 (10 cards of 10 tablets each).

The 50 mg tablets are orange film-coated, round, unscored tablets debossed with Mover 59on one side and 50on the other side. They are available as follows:

NDC 48433-097-20 – Unit dose blister packages of 100 (10 cards of 10 tablets each).

The 100 mg tablets are orange film-coated, round, unscored tablets debossed with Mover 61on one side and 100on the other side. They are available as follows:

NDC 48433-098-20 – Unit dose blister packages of 100 (10 cards of 10 tablets each).

Store at 20° to 25°C (68° to 77°F). [See USP Controlled Room Temperature.]
Protect from light.

**Trademark of Medical Economics Company, Inc.

Manufactured for:
Mylan Pharmaceuticals Inc.
Morgantown, WV 26505 U.S.A.

Manufactured by:
Mylan Laboratories Limited
Hyderabad — 500 096, India

Distributed by:
Safecor Health LLC
Rockford, IL 61103 U.S.A.

75108233

Revised: 1/2025
MX:THIO:R2

PRINCIPAL DISPLAY PANEL – 10 mg

NDC 48433-095-20

Thioridazine
Hydrochloride
Tablets, USP
10 mg

100 Tablets (10 x 10)

Each film-coated tablet contains:
Thioridazine hydrochloride, USP 10 mg

Usual Dosage:See accompanying
prescribing information.

Store at 20° to 25°C (68° to 77°F). [See
USP Controlled Room Temperature.]
Protect from light.

Code No.: MH/DRUGS/25/NKD/89

Manufactured for:
Mylan Pharmaceuticals Inc.
Morgantown, WV 26505 U.S.A.

Made in India

Rx only

S-13387

Distributed by:

Safecor Health LLC

Rockford, IL 61103 U.S.A.

This unit dose package is not child resistant.

For institutional use only.

Keep this and all drugs out of the reach of children.

This container provides light-resistance.

See window for lot number and expiration date.

PRINCIPAL DISPLAY PANEL – 25 mg

NDC 48433-096-20

Thioridazine
Hydrochloride
Tablets, USP
25 mg

100 Tablets (10 x 10)

Each film-coated tablet contains:
Thioridazine hydrochloride, USP 25 mg

Usual Dosage:See accompanying
prescribing information.

Store at 20° to 25°C (68° to 77°F). [See
USP Controlled Room Temperature.]
Protect from light.

Code No.: MH/DRUGS/25/NKD/89

Manufactured for:
Mylan Pharmaceuticals Inc.
Morgantown, WV 26505 U.S.A.

Made in India

Rx only

S-13390

Distributed by:

Safecor Health LLC

Rockford, IL 61103 U.S.A.

This unit dose package is not child resistant.

For institutional use only.

Keep this and all drugs out of the reach of children.

This container provides light-resistance.

See window for lot number and expiration date.

PRINCIPAL DISPLAY PANEL – 50 mg

NDC 48433-097-20

Thioridazine
Hydrochloride
Tablets, USP
50 mg

100 Tablets (10 x 10)

Each film-coated tablet contains:
Thioridazine hydrochloride, USP 50 mg

Usual Dosage:See accompanying
prescribing information.

Store at 20° to 25°C (68° to 77°F). [See
USP Controlled Room Temperature.]
Protect from light.

Code No.: MH/DRUGS/25/NKD/89

Manufactured for:
Mylan Pharmaceuticals Inc.
Morgantown, WV 26505 U.S.A.

Made in India

Rx only

S-13395

Distributed by:

Safecor Health LLC

Rockford, IL 61103 U.S.A.

This unit dose package is not child resistant.

For institutional use only.

Keep this and all drugs out of the reach of children.

This container provides light-resistance.

See window for lot number and expiration date.

PRINCIPAL DISPLAY PANEL – 100 mg

NDC 48433-098-20

Thioridazine
Hydrochloride
Tablets, USP
100 mg

100 Tablets (10 x 10)

Each film-coated tablet contains:
Thioridazine hydrochloride, USP 100 mg

Usual Dosage:See accompanying
prescribing information.

This strength tablet is for use only in
severe neuropsychiatric conditions.

Store at 20° to 25°C (68° to 77°F). [See
USP Controlled Room Temperature.]
Protect from light.

Code No.: MH/DRUGS/25/NKD/89

Manufactured for:
Mylan Pharmaceuticals Inc.
Morgantown, WV 26505 U.S.A.

Made in India

Rx only

S-13400

Distributed by:

Safecor Health LLC

Rockford, IL 61103 U.S.A.

This unit dose package is not child resistant.

For institutional use only.

Keep this and all drugs out of the reach of children.

This container provides light-resistance.

See window for lot number and expiration date.